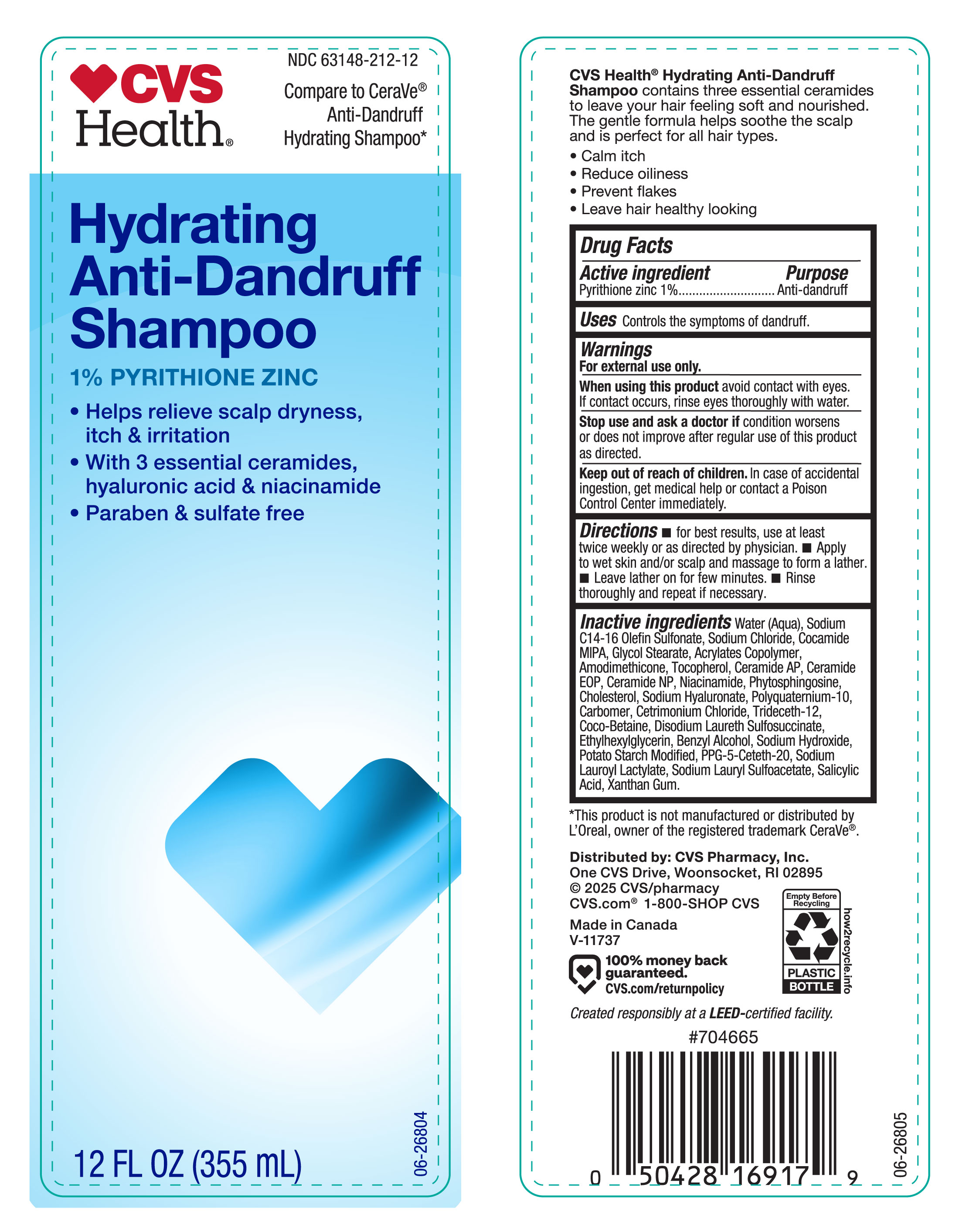 DRUG LABEL: CVS ANTI DANDRUFF
NDC: 63148-212 | Form: SHAMPOO
Manufacturer: Apollo Health and Beauty Care
Category: otc | Type: HUMAN OTC DRUG LABEL
Date: 20251013

ACTIVE INGREDIENTS: PYRITHIONE ZINC 10 mg/1 mL
INACTIVE INGREDIENTS: SODIUM CHLORIDE; COCO-BETAINE; CERAMIDE 9; WATER; POLYQUATERNIUM-10 (400 CPS AT 2%); CETRIMONIUM CHLORIDE; SODIUM HYDROXIDE; COCAMIDE MIPA; DISODIUM LAURETH SULFOSUCCINATE; GLYCOL STEARATE; SALICYLIC ACID; SODIUM C14-16 OLEFIN SULFONATE; NIACINAMIDE; CERAMIDE AP; CERAMIDE NP; SODIUM LAUROYL LACTYLATE; PHYTOSPHINGOSINE; ETHYLHEXYLGLYCERIN; CHOLESTEROL; TOCOPHEROL; PPG-5-CETETH-20; TRIDECETH-12; ACRYLATES/VINYL ISODECANOATE CROSSPOLYMER (10000 MPA.S NEUTRALIZED AT 0.5%); SODIUM LAURYL SULFOACETATE; AMODIMETHICONE (240 CST); CARBOMER; XANTHAN GUM; STARCH, POTATO; BENZYL ALCOHOL; SODIUM HYALURONATE

NDC-63148-212-12, CVS ANTI DANDRUFF SHAMPOO

Active Ingredient

Pyrithione Zinc (1%)

Purpose

Anti-dandruff.

Uses

Controls the symptoms of dandruff.

Warnings

For external use only

When using this product

avoid contact with eyes. If contact occurs, rise eyes thoroughly with water.

Stop use and ask a doctor if

condition worsen or does not improve after regular use of this product as directed.

Keep out of reach of children.

In case of accidental ingestion, get medical help or contact a Poison Comtrol Center immediately.

Directions

- for best results, use at least twice weekly or as directed by the physician.
- Apply to wet skin and/or scalp and massage to form a lather.
- Leave lather on for few minutes.
- Rinse thoroughly and repeat if necessary.

Inactive Ingredients

Water (Aqua), Sodium C14-16 Olefin Sulfonate, Sodium Chloride, Cocamide MIPA, Glycol Stearate, Acrylates Copolymer, Amodimethicone, Tocopherol, Ceramide AP, Ceramide EOP, Ceramide NP, Niacinamide, Phytospingosine, Chlesterol, Sodium Hyaluronate, Polyquaternium-10, Carbomer, Cetrimonium Chloride, Trideceth-12, Coco-Betaine, Disodium Laureth Sulfosuccinate, Ethylhexylglycerin, Benzyl Alcohol, Sodium Hydroxide, Potato Starch Modified, PPG-5-Ceteth-20, Sodium Lauroyl Lactylate, Sodium Lauryl Sulfoacetate, Salicylic Acid, Xanthan Gum.